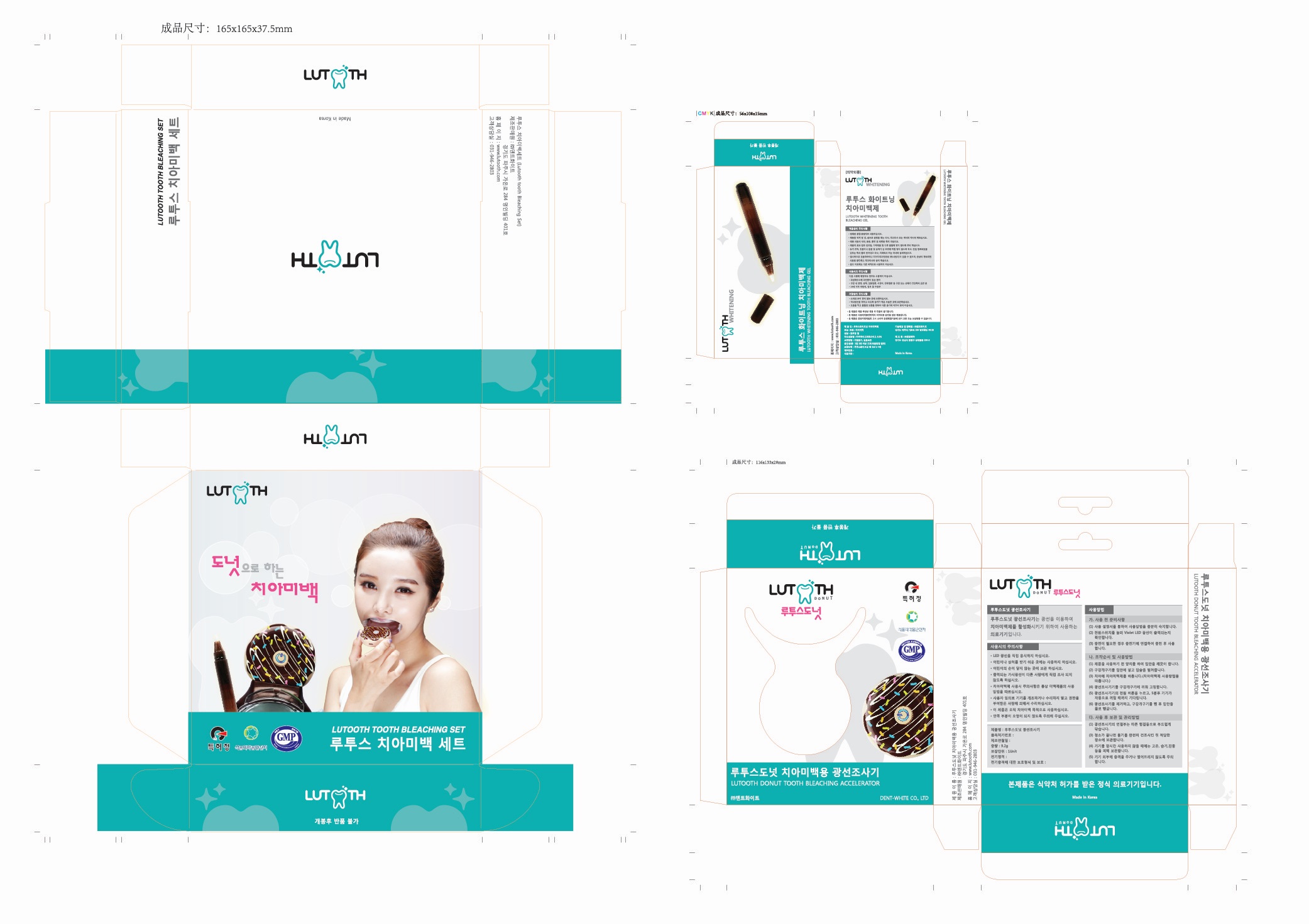 DRUG LABEL: Lutooth Tooth Whitening Kit
NDC: 70635-0003 | Form: GEL, DENTIFRICE
Manufacturer: Quorum Bio CO.,LTD
Category: otc | Type: HUMAN OTC DRUG LABEL
Date: 20201014

ACTIVE INGREDIENTS: CARBAMIDE PEROXIDE 15 g/100 mL
INACTIVE INGREDIENTS: WATER

ACTIVE INGREDIENT

Carbamide Peroxide 15%

INACTIVE INGREDIENT

Water, etc.

PURPOSE

Tooth whitening

WARNINGS

Persons who CANNOT use Lutooth whitening kit.

- To be on the safe side, pregnant and breastfeeding women, children under the age of 14 should postpone tooth whitening.
- DO NOT use if teeth or gum are not healthy.
- Avoid ingestion and contact with eyes and skin. If contact occurs, wipe gel off and rinse with water.
- The LED device should not be used for other purpose.
- If sensitivity or gum irritation occurs, please stop using whitening gel and consult your dentist.

KEEP OUT OF REACH OF CHILDREN

Keep out of reach of babies and children.

INDICATIONS AND USAGE

Tooth Whitening Procedure & Method

You can find video clips of 'How to Use' at Lutooth hompage (http://www.lutooth.com)

For detailed descriptions, plase refer to the user manual inside the product package.

1. Exercise of installation
2. The Use of Whitening Stick
3. Put Cotton rolls
4. Put the lip&cheek retractor
5. Wipe saliva with the cotton roll
6. Apply whitening gels
7. Installation & Operation of LED Accelerator
8. Finishing 1 Cycle
9. Repeat (Three cycles a day)
10. Turn on LED light without whitening gels (Optional)

DOSAGE AND ADMINISTRATION

- If you want rapid effects, repeat 12 cycles (it takes one hour) or until desired whitening results are achieved.
- For the best effect, it is preferable to carry out every day for 4 days.
- Then, repeat the whitening cycle again for 4 days after 2 or 3 days break.